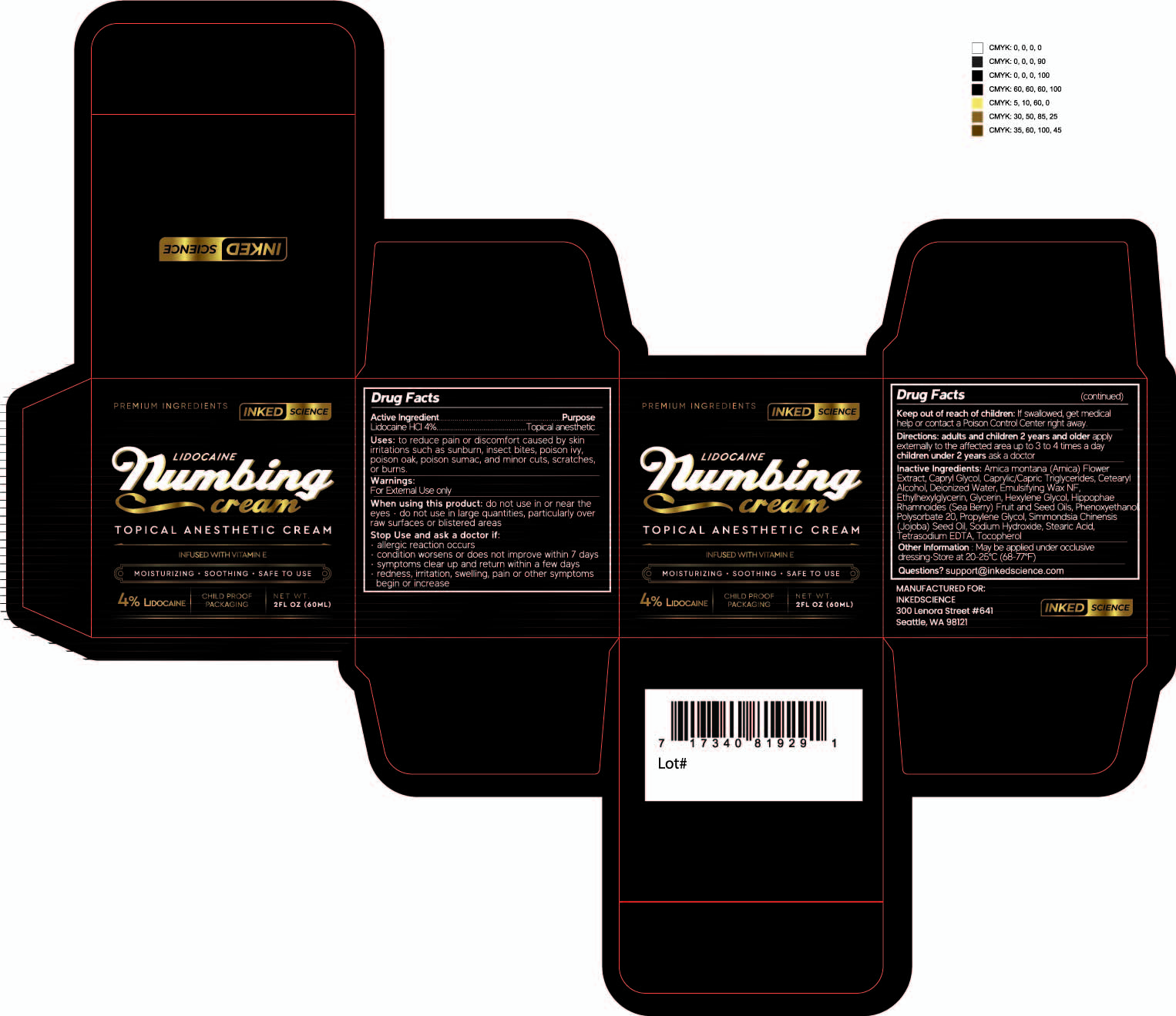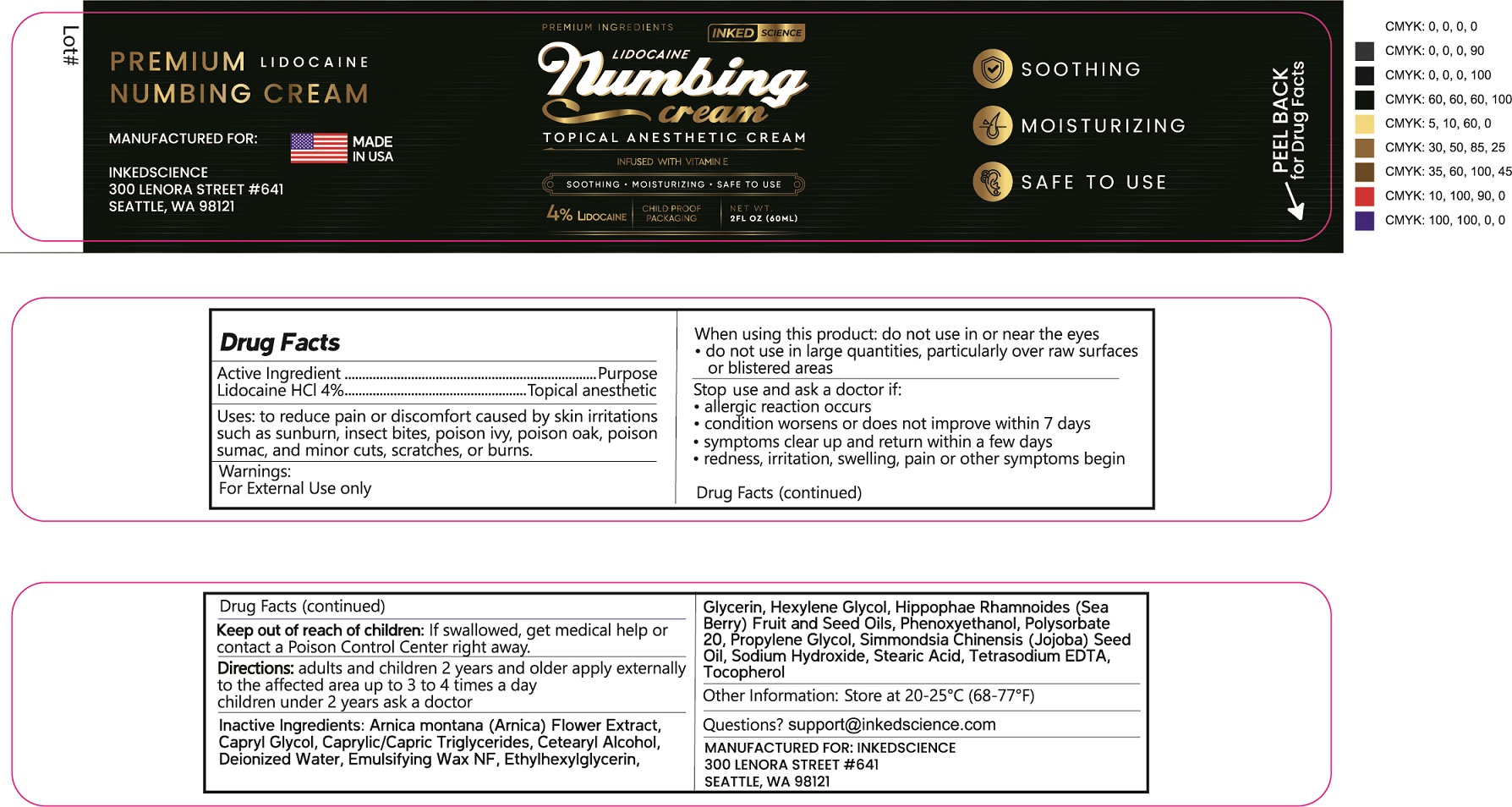 DRUG LABEL: INKED SCIENCE LIDOCAINE 4 Percent
NDC: 76348-960 | Form: CREAM
Manufacturer: RENU LABORATORIES, INC.
Category: otc | Type: HUMAN OTC DRUG LABEL
Date: 20220225

ACTIVE INGREDIENTS: LIDOCAINE HYDROCHLORIDE 2.24 g/56 g
INACTIVE INGREDIENTS: HEXYLENE GLYCOL; HIPPOPHAE RHAMNOIDES SEED OIL; WATER; MEDIUM-CHAIN TRIGLYCERIDES; PROPYLENE GLYCOL; JOJOBA OIL; CETOSTEARYL ALCOHOL; ARNICA MONTANA FLOWER; CAPRYLYL GLYCOL; ETHYLHEXYLGLYCERIN; STEARIC ACID; TOCOPHEROL; POLYSORBATE 20; HIPPOPHAE RHAMNOIDES FRUIT OIL; GLYCERIN; PHENOXYETHANOL; SODIUM HYDROXIDE; EDETATE SODIUM; WHITE WAX

Inked Science LIDOCAINE NUMBING CREAM

STATEMENT OF IDENTITY

INKED SCIENCE LIDOCAINE NUMBING CREAM

ACTIVE INGREDIENT

Lidocaine HCl 4%

Purpose

Topical anesthetic

INDICATIONS AND USAGE

Uses: to reduce pain or discomfort caused by skin irritations such as sunburn, insect bites, poison ivy, poison oak, poison sumac, and minor cuts, scratches or burns.

WARNINGS

For External Use only

When using this product, do not use in or near the eyes

- do not use in large quantities, particularly over raw surfaces or blistered areas.

Stop Use and ask a doctor if:

- allergic reaction occurs
- condition worsens or does not improve within 7 days
- symptoms clear up and return within a few days
- redness, irritation, swelling, pain or other symptoms begin.

Keep out of reach of children. If swallowed, get medical help or contact a Poison Control Center right away.

DOSAGE AND ADMINISTRATION

Directions: adults and children 2 years and older apply externally to the affected area up to 3 to 4 times a day

Children under 2 years, ask a doctor

OTHER SAFETY INFORMATION

Store at 20 - 25° C

QUESTIONS

support@inkedscience.com

INACTIVE INGREDIENT

Arnica Montana Extract, Capryl Glycol, Caprylic/Capric Triglycerides, Cetearyl Alcohol, Deionized Water, Emulsifying Wax NF, Ethylhexylglycerin, Glycerin,Hexylene Glycol, Hippophae Rhamnoides Fruit and Seed Oils, Phenoxyethanol, Polysorbate 20, Propylene Glycol, Simmondsia Chinensis (Jojoba) Seed Oil, Sodium Hydroxide, Stearic Acid, Tetrasodium EDTA, Tocopherol

RECENT MAJOR CHANGES

INDICATIONS AND USAGE Only a date change due to creation of a CLONE SPL.

DOSAGE and ADMINISTRATION Only a date change due to creation of a CLONE SPL

PRODUCT LABEL AND PRODUCT BOX